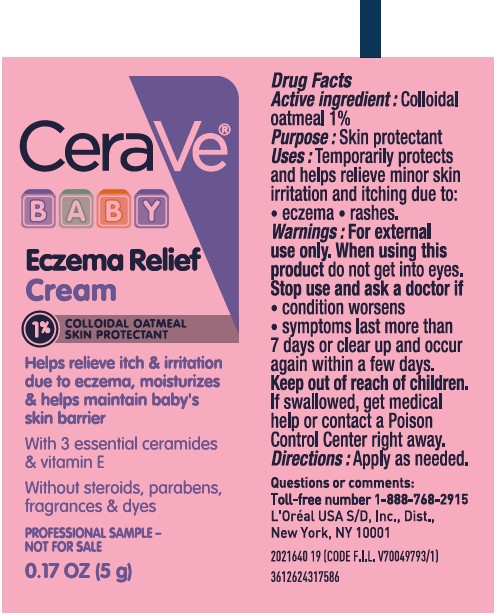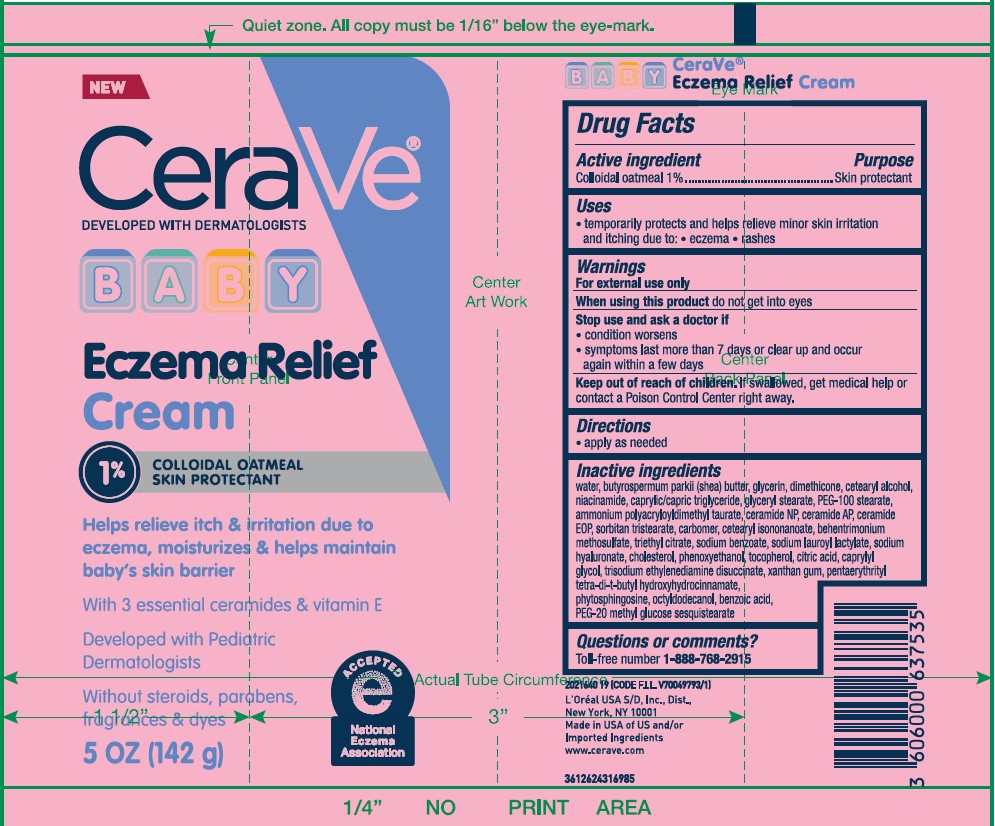 DRUG LABEL: CeraVe Developed With Dermatologist Baby Eczema Relief Cream
NDC: 49967-536 | Form: CREAM
Manufacturer: L'Oreal USA Products Inc
Category: otc | Type: HUMAN OTC DRUG LABEL
Date: 20251209

ACTIVE INGREDIENTS: OATMEAL 10 mg/1 mL
INACTIVE INGREDIENTS: WATER; BUTYROSPERMUM PARKII (SHEA) BUTTER; GLYCERIN; DIMETHICONE; CETEARYL ALCOHOL; NIACINAMIDE; CAPRYLIC/CAPRIC TRIGLYCERIDE; GLYCERYL STEARATE; PEG-100 STEARATE; AMMONIUM POLYACRYLOYLDIMETHYL TAURATE; CERAMIDE NP; CERAMIDE AP; SORBITAN TRISTEARATE; CARBOMER; CETEARYL ISONONANOATE; BEHENTRIMONIUM METHOSULFATE; TRIETHYL CITRATE; SODIUM BENZOATE; SODIUM LAUROYL LACTYLATE; SODIUM HYALURONATE; CHOLESTEROL; PHENOXYETHANOL; TOCOPHEROL; CITRIC ACID; CAPRYLYL GLYCOL; TRISODIUM ETHYLENEDIAMINE DISUCCINATE; XANTHAN GUM; PENTAERYTHRITYL TETRA-DI-T-BUTYL HYDROXYHYDROCINNAMATE; PHYTOSPHINGOSINE; OCTYLDODECANOL; BENZOIC ACID; PEG-20 METHYL GLUCOSE SESQUISTEARATE

Drug Facts

Active ingredient

Colloidal oatmeal 1%

Purpose

Skin protectant

Uses

- temporarily protects and helps relieve minor skin irritation and itching due to: •eczema •rashes

Warnings

For external use only

When using this product

do not get into eyes

Stop use and ask a doctor if

- condition worsens
- symptoms last more than 7 days or clear up and occur again within a few days

Keep out of reach of children.

If swallowed, get medical help or contact a Poison Control Center right away.

Directions

apply as needed

Inactive ingredients

water, butyrospermum parkii (shea) butter, glycerin, dimethicone, cetearyl alcohol, niacinamide, caprylic/capric triglyceride, glyceryl stearate, PEG-100 stearate, ammonium polyacryloyldimethyl taurate, ceramide np, ceramide ap, ceramide eop, sorbitan tristearate, carbomer, cetearyl isononanoate, behentrimonium methosulfate, triethyl citrate, sodium benzoate, sodium lauroyl lactylate, sodium hyaluronate, cholesterol, phenoxyethanol, tocopherol, citric acid, caprylyl glycol, trisodium ethylenediamine disuccinate, xanthan gum, pentaerythrityl tetra-di-t-butyl hydroxyhydrocinnamate, phytosphingosine, octyldodecanol, benzoic acid, PEG-20 methyl glucose sesquistearate

Questions or comments?

Toll-free number 1-888-768-2915